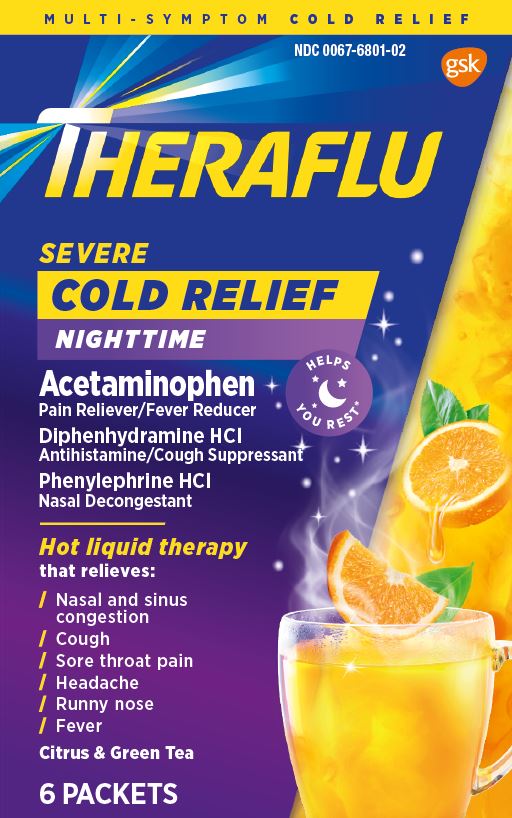 DRUG LABEL: Theraflu Severe Cold relief Nighttime
NDC: 0067-6801 | Form: POWDER
Manufacturer: Haleon US Holdings LLC
Category: otc | Type: HUMAN OTC DRUG LABEL
Date: 20240308

ACTIVE INGREDIENTS: ACETAMINOPHEN 500 mg/1 1; DIPHENHYDRAMINE HYDROCHLORIDE 25 mg/1 1; PHENYLEPHRINE HYDROCHLORIDE 10 mg/1 1
INACTIVE INGREDIENTS: ACESULFAME POTASSIUM; ANHYDROUS CITRIC ACID; ASPARTAME; FD&C YELLOW NO. 6; MALTODEXTRIN; SILICON DIOXIDE; SODIUM CITRATE, UNSPECIFIED FORM; LECITHIN, SOYBEAN; SUCROSE; TRIBASIC CALCIUM PHOSPHATE

Drug Facts

Active ingredients (in each packet)

Acetaminophen 500 mg

Diphenhydramine HCl 25 mg

Phenylephrine HCl 10 mg

Purposes

Pain reliever/Fever reducer

Antihistamine/cough suppressant

Nasal decongestant

Uses

- temporarily relieves these symptoms due to a cold:
  - minor aches and pains
  - minor sore throat pain
  - headache
  - nasal and sinus congestion
  - runny nose
  - sneezing
  - itchy nose or throat
  - itchy, watery eyes due to hay fever
  - cough due to minor throat and bronchial irritation
- temporarily reduces fever

Warnings

Liver warning:This product contains acetaminophen. Severe liver damage may occur if you take

- more than 4,000 mg of acetaminophen in 24 hours
- with other drugs containing acetaminophen
- 3 or more alcoholic drinks every day while using this product

Allergy alert:Acetaminophen may cause severe skin reactions. Symptoms may include:

- skin reddening
- blisters
- rash
- If a skin reaction occurs, stop use and seek medical help right away.

Sore throat warning:If sore throat is severe, persists for more than 2 days, is accompanied or followed by fever, headache, rash, nausea, or vomiting consult a doctor promptly.

Do Not Use

- in a child under 12 years of age
- if you are allergic to acetaminophen
- with any other drug containing acetaminophen (prescription or nonprescription). If you are not sure whether a drug contains acetaminophen, ask a doctor or pharmacist.
- with any other product containing diphenhydramine, even one used on the skin
- if you are now taking a prescription monoamine oxidase inhibitor (MAOI) (certain drugs for depression, psychiatric, or emotional conditions, or Parkinson’s disease), or for 2 weeks after stopping the MAOI drug. If you do not know if your prescription drug contains an MAOI, ask a doctor or pharmacist before taking this product.

Ask a doctor before use if you have

- liver disease
- heart disease
- high blood pressure
- thyroid disease
- diabetes
- glaucoma
- trouble urinating due to an enlarged prostate gland
- a breathing problem such as emphysema or chronic bronchitis
- cough that occurs with too much phlegm (mucus)
- cough that lasts or is chronic such as occurs with smoking, asthma or emphysema

Ask a doctor or pharmacist before use if you are

- taking sedatives or tranquilizers
- taking the blood thinning drug warfarin

When using this product

- do not exceed recommended dosage
- avoid alcoholic drinks
- marked drowsiness may occur
- alcohol, sedatives and tranquilizers may increase drowsiness
- be careful when driving a motor vehicle or operating machinery
- excitability may occur, especially in children

Stop use and ask a doctor if

- nervousness, dizziness, or sleeplessness occurs
- fever gets worse or lasts more than 3 days
- redness or swelling is present
- new symptoms occur
- pain, cough or nasal congestion gets worse or last more than 7 days
- cough comes back or occurs with rash or headache that lasts. These could be signs of a serious condition.

If pregnant or breast-feeding,

ask a health professional before use.

Keep out of reach of children.

In case of overdose, get medical help or contact a Poison Control Center right away. Prompt medical attention is critical for adults as well as for children even if you do not notice any signs or symptoms.

Directions

- do not use more than directed
- take every 4 hours, while symptoms persist. Do not take more than 6 packets in 24 hours unless directed by a doctor

1. Age

1. Dose

1. adults and children 12 years of age and over

1. one packet

1. children under 12 years of age

1. do not use

- dissolve contents of one packet into 8 oz. hot water; sip while hot. Consumer entire drink within 10-15 minutes.
- if using a microwave, add contents of one packet to 8 oz. of cool water; stir briskly before and after heating. Do not overheat.

Other information

- each packet contains: potassium 10 mg, sodium 23 mg
- phenylketonurics: contains phenylalanine 13 mg per packet
- store at controlled room temperature 20-25°C (68-77°F). Protect product from heat and moisture.

Inactive ingredients

acesulfame potassium, anhydrous citric acid, aspartame, FD&C yellow no. 6, flavors, maltodextrin, silicon dioxide, sodium citrate, soy lecithin, sucrose, tribasic calcium phosphate

Questions or Comments?

call 1-800-328-5259

Generic Section

TAMPER EVIDENT INNER UNIT
DO NOT USE IF SEALED THERAFLU PACKET IS TORN OR BROKEN

1-855-328-5259

Distributed by: GSK Consumer Healthcare
Warren, NJ 07059
©2022 GSK group of companies or its licensor.
Trademarks are owned by or licensed to the GSK group of companies. 62000000075407

HOT LIQUID THERAPY
that relieves:

Nasal and sinus congestion Cough

Sore throat pain Headache

Runny nose Fever

PARENTS:
Learn about teen medicine abuse
www.StopMedicineAbuse.com

*Temporarily controls cough to help you rest. This is not a sleep aid

CARTON
RECYCLE

Principal Display Panel

NDC 0067-6801-02

MULTI-SYMPTOM COLD RELIEF

THERAFLU

SEVERE

COLD RELIEF

NIGHTTIME

ACETAMINOPHEN
PAIN RELIEVER/FEVER REDUCER

DIPHENHYDRAMINE HCl
ANTIHISTAMINE/COUGH SUPPRESSANT

PHENYLEPHRINE HCl
NASAL DECONGESTANT

HELPS YOU REST*

Hot liquid therapy
that relieves:

/Nasal and sinus congestion
/ Cough
/ Sore throat pain
/ Headache
/ Runny nose
/ Fever

Citrus & Green Tea

6 PACKETS